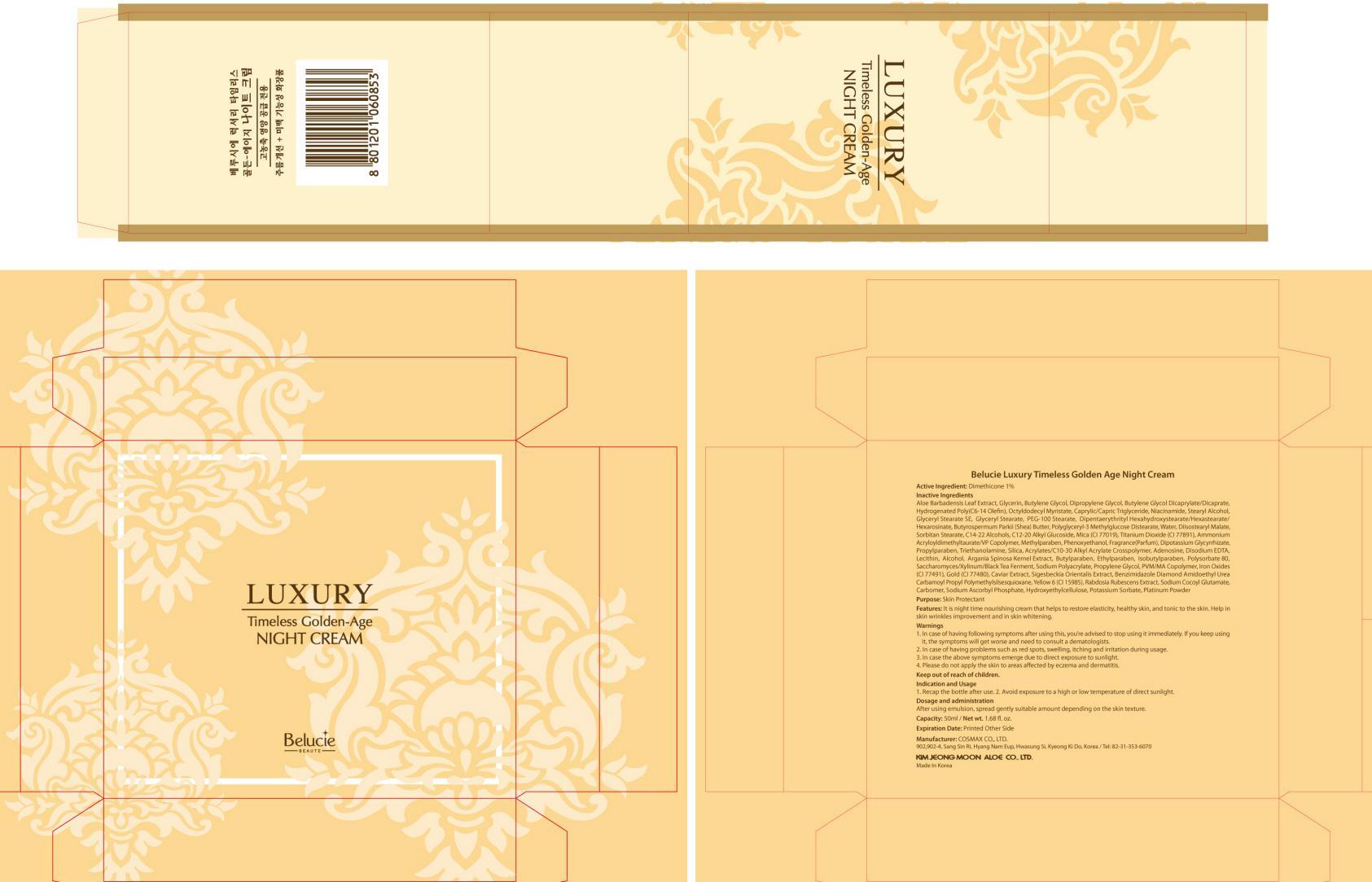 DRUG LABEL: Belucie Luxury Timeless Golden Age Night
NDC: 50410-070 | Form: CREAM
Manufacturer: KIMJEONGMOON ALOE CO., LTD.
Category: otc | Type: HUMAN OTC DRUG LABEL
Date: 20121130

ACTIVE INGREDIENTS: Dimethicone 0.5 g/50 mL
INACTIVE INGREDIENTS: ALOE VERA LEAF; Glycerin; Butylene Glycol; Dipropylene Glycol

ACTIVE INGREDIENT

Active Ingredient: Dimethicone 1%

INACTIVE INGREDIENT

Inactive Ingredients:
Aloe Barbadensis Leaf Extract, Glycerin, Butylene Glycol, Dipropylene Glycol, Butylene Glycol Dicaprylate/Dicaprate, Hydrogenated Poly(C6-14 Olefin), Octyldodecyl Myristate, Caprylic/Capric Triglyceride, Niacinamide, Stearyl Alcohol, Glyceryl Stearate SE, Glyceryl Stearate, PEG-100 Stearate, Dipentaerythrityl Hexahydroxystearate/Hexastearate/Hexarosinate, Butyrospermum Parkii (Shea) Butter, Polyglyceryl-3 Methylglucose Distearate, Water, Diisostearyl Malate, Sorbitan Stearate, C14-22 Alcohols, C12-20 Alkyl Glucoside, Mica (CI 77019), Titanium Dioxide (CI 77891), Ammonium Acryloyldimethyltaurate/VP Copolymer, Methylparaben, Phenoxyethanol, Fragrance(Parfum), Dipotassium Glycyrrhizate, Propylparaben, Triethanolamine, Silica, Acrylates/C10-30 Alkyl Acrylate Crosspolymer, Adenosine, Disodium EDTA, Lecithin, Alcohol, Argania Spinosa Kernel Extract, Butylparaben, Ethylparaben, Isobutylparaben, Polysorbate 80, Saccharomyces/Xylinum/Black Tea Ferment, Sodium Polyacrylate, Propylene Glycol, PVM/MA Copolymer, Iron Oxides (CI 77491), Gold, Caviar Extract, Sigesbeckia Orientalis Extract, Benzimidazole Diamond Amidoethyl Urea Carbamoyl Propyl Polymethylsilsesquioxane, Yellow 6, Rabdosia Rubescens Extract, Sodium Cocoyl Glutamate, Carbomer, Sodium Ascorbyl Phosphate, Hydroxyethylcellulose, Potassium Sorbate, Platinum Powder

PURPOSE

Purpose: Skin Protectant

WARNINGS

1. In case of having following symptoms after using this, you’re advised to stop using it immediately. If you keep using it, the symptoms will get worse and need to consult a dematologists.
2. In case of having problems such as red spots, swelling, itching and irritation during usage
3. In case the above symptoms emerge due to direct exposure to sunlight
4. Please do not apply the skin to areas affected by eczema and dermatitis

KEEP OUT OF REACH OF CHILDREN

INDICATIONS AND USAGE

Indication and usage
1. Recap the bottle after use.
2. Avoid exposure to a high or low temperature of direct sunlight

DOSAGE AND ADMINISTRATION

After using emulsion, spread gently suitable amount depending on the skin texture.